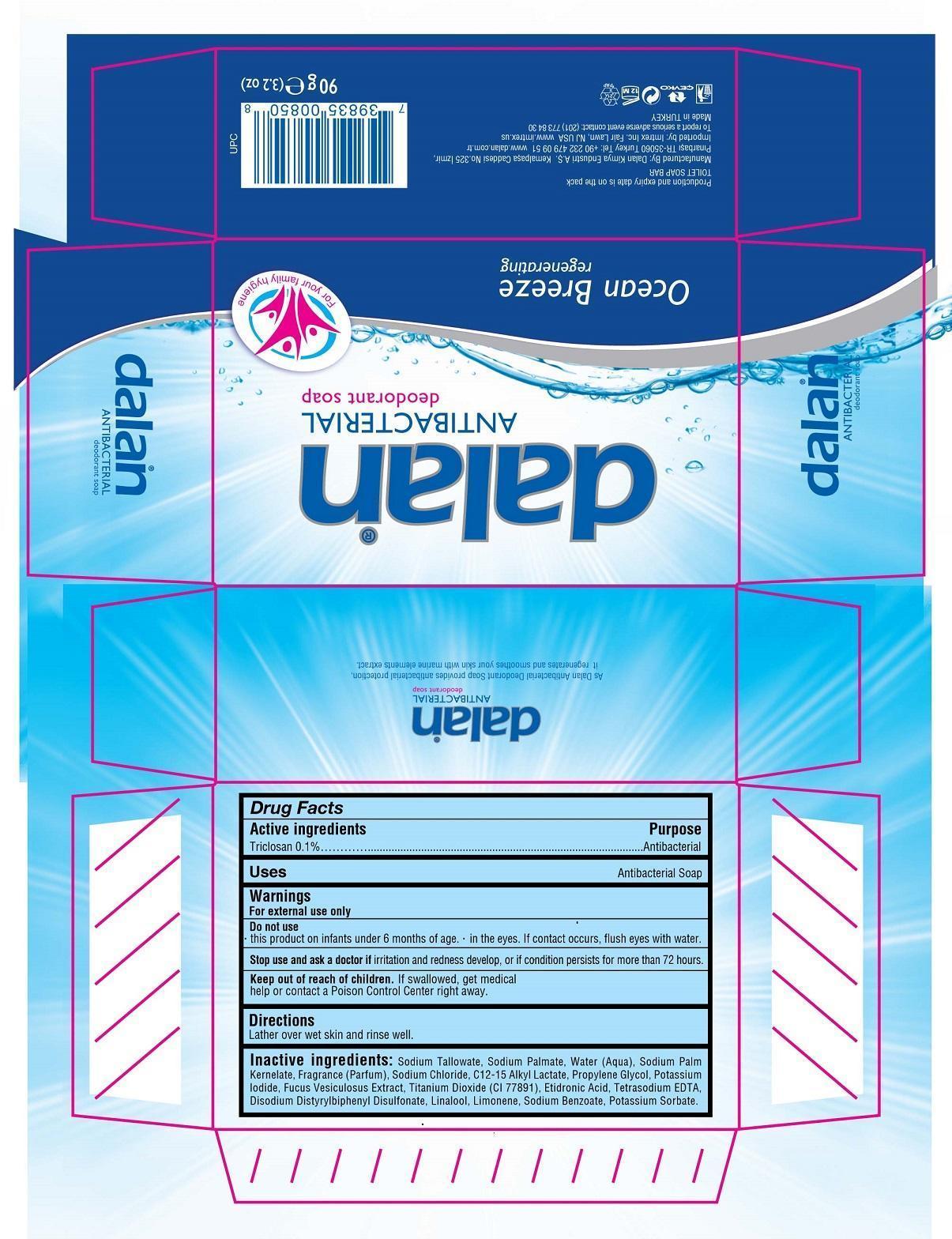 DRUG LABEL: dalan ANTIBACTERIAL deodorant Ocean Breeze regenerating
NDC: 51209-005 | Form: SOAP
Manufacturer: Dalan Kimya Endustri A.S.
Category: otc | Type: HUMAN OTC DRUG LABEL
Date: 20160212

ACTIVE INGREDIENTS: TRICLOSAN 0.1 g/100 g
INACTIVE INGREDIENTS: SODIUM PALMATE; WATER; SODIUM PALM KERNELATE; SODIUM CHLORIDE; C12-15 ALKYL LACTATE; PROPYLENE GLYCOL; POTASSIUM IODIDE; FUCUS VESICULOSUS; TITANIUM DIOXIDE; ETIDRONIC ACID; EDETATE SODIUM; LINALOOL, (+/-)-; SODIUM BENZOATE; POTASSIUM SORBATE

dalan ANTIBACTERIAL deodorant soap Ocean Breeze regenerating

Active ingredients

Triclosan 0.1%

Purpose

Antibacterial

Uses

Antibacterial Soap

Warnings

For external use only

Do not use

this product on infants under 6 months of age.

in the eyes. If contact occurs, flush eyes with water.

Stop use and ask a doctor if

irritation and redness develop, or if condition persists for more than 72 hours.

Keep out of reach of children.

If swallowed, get medical help or contact a Poison Control Center right away.

Directions

Lather over wet skin and rinse well.

Inactive ingredients:

Sodium Tallowate, Sodium Palmate, Water (Aqua), Sodium Palm Kernelate, Fragrance (Parfum), Sodium Chloride, C12-15 Alkyl Lactate, Propylene Glycol, Potassium Iodide, Fucus Vesiculosus Extract, Titanium Dioxide (CI 77891), Etidronic Acid, Tetrasodium EDTA, Disodium Distyrylbiphenyl Disulfonate, Linalool, Limonene, Sodium Benzoate, Potassium Sorbate.